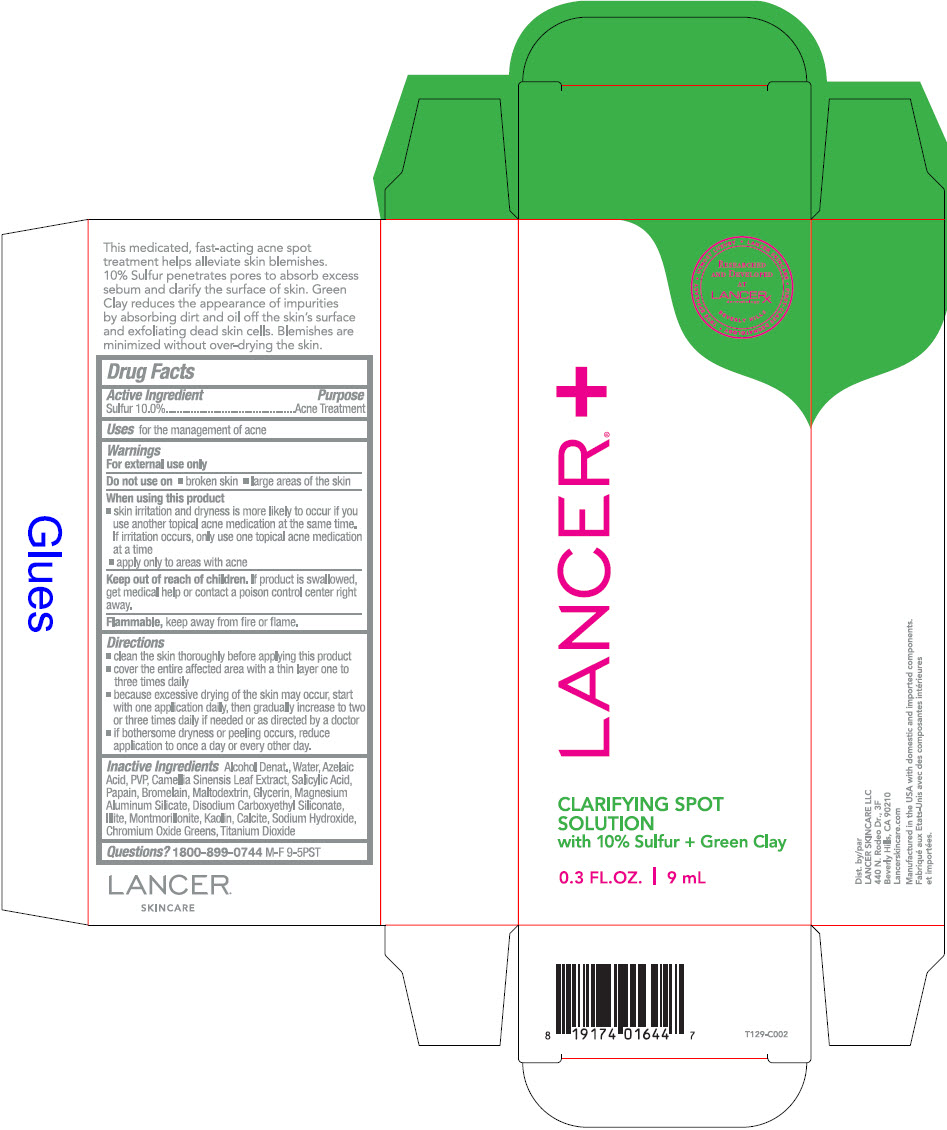 DRUG LABEL: Clarifying Spot with Sulfur plus Green Clay 
NDC: 72704-129 | Form: SOLUTION
Manufacturer: Lancer Skincare LLC.
Category: otc | Type: HUMAN OTC DRUG LABEL
Date: 20230119

ACTIVE INGREDIENTS: Sulfur 10 g/100 mL
INACTIVE INGREDIENTS: Alcohol; Water; Azelaic Acid; POVIDONE, UNSPECIFIED; Green Tea Leaf; Salicylic Acid; Papain; Bromelains; Maltodextrin; Glycerin; Magnesium Aluminum Silicate; Disodium Carboxyethyl Siliconate; Ledikite; Montmorillonite; Kaolin; Calcium Carbonate; Sodium Hydroxide; Chromic Oxide; Titanium Dioxide

Clarifying Spot with Sulfur plus Green Clay
Acne Medication

Drug Facts

Active Ingredient

Sulfur 10.0%

Purpose

Acne Treatment

Uses

For the management of acne

Warnings

For external use only

Do not use on

- Broken skin
- Large areas of the skin

When using this product

- skin irritation and dryness is more likely to occur if you use another topical acne medication at the same time. If irritation occurs, only use one topical acne medication at a time
- apply only to areas with acne

Keep out of reach of children. If product is swallowed, get medical help or contact a poison control center right away.

Flammable, keep away from fire or flame.

Directions

- clean the skin thoroughly before applying this product
- cover the entire affected area with a thin layer one to three times daily
- because excessive drying of the skin may occur, start with one application daily, then gradually increase to two or three times daily if needed or as directed by a doctor
- if bothersome dryness or peeling occurs, reduce application to once a day or every other day.

Inactive Ingredients

Alcohol Denat., Water, Azelaic Acid, PVP, Camellia Sinensis Leaf Extract, Salicylic Acid, Papain, Bromelain, Maltodextrin, Glycerin, Magnesium Aluminum Silicate, Disodium Carboxyethyl Siliconate, Illite, Montmorillonite, Kaolin, Calcite, Sodium Hydroxide, Chromium Oxide Greens, Titanium Dioxide

Questions?

1800-899-0744 M-F 9-5PST

Dist. by
LANCER SKINCARE LLC
440 N. Rodeo Dr., 3F
Beverly Hills, CA 90210

PRINCIPAL DISPLAY PANEL - 9 mL Tube Carton

LANCER®

RESEARCHED
AND DEVELOPED
AT
LANCERX™
dermatology
BEVERLY HILLS

• UTMOST LUXURY
• LANCER SKINCARE
• FIRST-CLASS DERMATOLOGY
• TRUE EFFICACY

CLARIFYING SPOT
SOLUTION
with 10% Sulfur + Green Clay

0.3 FL.OZ. | 9 mL